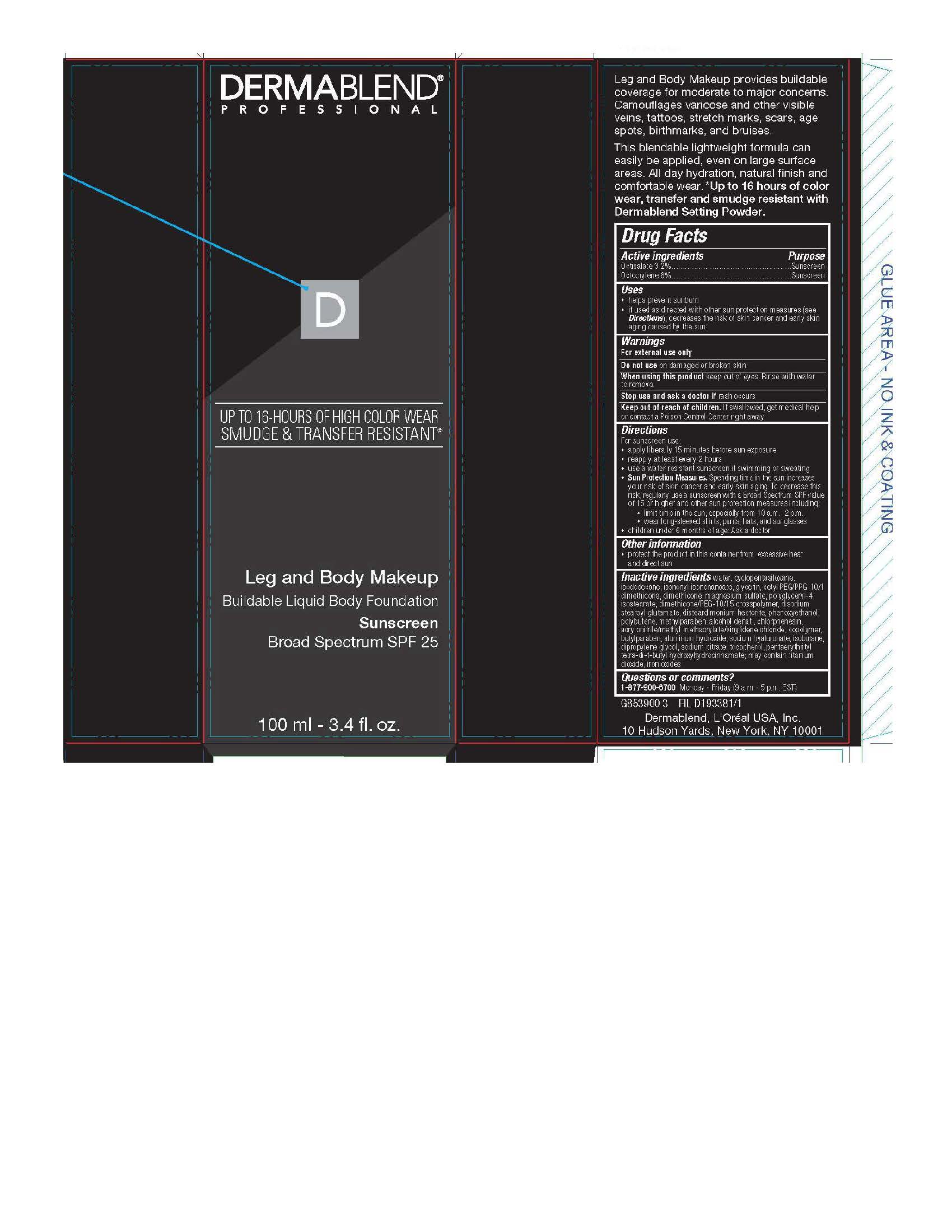 DRUG LABEL: Leg and Body Makeup Broad Spectrum SPF 25
NDC: 84203-002 | Form: LIQUID
Manufacturer: Baxter of California, LLC
Category: otc | Type: HUMAN OTC DRUG LABEL
Date: 20250724

ACTIVE INGREDIENTS: OCTISALATE 32 mg/1 mL; OCTOCRYLENE 60 mg/1 mL
INACTIVE INGREDIENTS: DISTEARDIMONIUM HECTORITE; BUTYLPARABEN; HYALURONATE SODIUM; WATER; CYCLOMETHICONE 5; ISONONYL ISONONANOATE; POLYGLYCERYL-4 ISOSTEARATE; METHYLPARABEN; CHLORPHENESIN; DIPROPYLENE GLYCOL; FERRIC OXIDE RED; ISODODECANE; GLYCERIN; CETYL PEG/PPG-10/1 DIMETHICONE (HLB 2); DIMETHICONE; ALCOHOL; TOCOPHEROL; PENTAERYTHRITOL TETRAKIS(3-(3,5-DI-TERT-BUTYL-4-HYDROXYPHENYL)PROPIONATE); TITANIUM DIOXIDE; DISODIUM STEAROYL GLUTAMATE; PHENOXYETHANOL; POLYBUTENE (1400 MW); ISOBUTANE; ALUMINUM HYDROXIDE; SODIUM CITRATE

Dermablend Leg and Body Makeup Broad Spectrum SPF 25

Active ingredients

Octisalate 3.2%

Octocrylene 6%

Purpose

Sunscreen

Uses

helps prevent sunburn - if used as directed with other sun protection measures (see Directions), decreases the risk of skin cancer and early skin aging caused by the sun

WARNINGS

For external use only

Do not use

on damaged or broken skin

When using this product

keep out of eyes. Rinse with water to remove.

Keep out of reach of children.

If swallowed, get medical help or contact a Poison Control Center right away.

Stop use and ask a doctor if

rash occurs

Directions

For sunscreen use: ● apply liberally 15 minutes before sun exposure ● reapply at least every 2 hours ● use a water resistant sunscreen if swimming or sweating ● Sun Protection Measures. Spending time in the sun increases your risk of skin cancer and early skin aging. To decrease this risk, regularly use a sunscreen with a Broad Spectrum SPF value of 15 or higher and other sun protection measures including: ● limit time in the sun, especially from 10 a.m. – 2 p.m. ● wear long-sleeved shirts, pants, hats, and sunglasses ● children under 6 months of age: Ask a doctor

Other information

protect the product in this container from excessive heat and direct sun

Inactive ingredients

water, cyclopentasiloxane, isododecane, isononyl isononanoate, glycerin, cetyl PEG/PPG 10/1 dimethicone, dimethicone, magnesium sulfate, polyglyceryl-4 isostearate, dimethicone/PEG-10/15 crosspolymer, disodium stearoyl glutamate, disteardimonium hectorite, phenoxyethanol, polybutene, methylparaben, alcohol denat., chlorphenesin, acrylonitrile/methyl methacrylate/vinylidene chloride copolymer, butylparaben, aluminum hydroxide, sodium hydroxide, isobutane, dipropylene glycol, sodium citrate, tocopherol, pentaerythrityl tetra-di-t-butyl hydroxyhydrocinnamate; may contain: titanium dioxide, iron oxides

QUESTIONS

1-877-900-6700 Monday - Friday (9 a.m. - 5 p.m. EST)